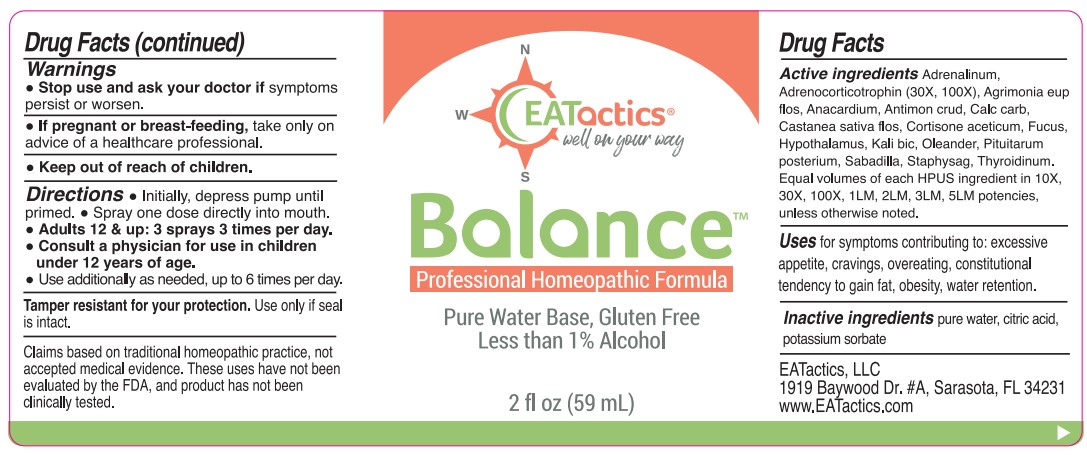 DRUG LABEL: Balance
NDC: 83665-001 | Form: SPRAY
Manufacturer: EATactics, LLC
Category: homeopathic | Type: HUMAN OTC DRUG LABEL
Date: 20230920

ACTIVE INGREDIENTS: FUCUS VESICULOSUS 10 [hp_X]/59 mL; EPINEPHRINE 10 [hp_X]/59 mL; CORTICOTROPIN 30 [hp_X]/59 mL; CASTANEA SATIVA FLOWER 10 [hp_X]/59 mL; CORTISONE ACETATE 10 [hp_X]/59 mL; OYSTER SHELL CALCIUM CARBONATE, CRUDE 10 [hp_X]/59 mL; NERIUM OLEANDER LEAF 10 [hp_X]/59 mL; SUS SCROFA PITUITARY GLAND, POSTERIOR 10 [hp_X]/59 mL; THYROID, UNSPECIFIED 10 [hp_X]/59 mL; ANTIMONY TRISULFIDE 10 [hp_X]/59 mL; BOS TAURUS HYPOTHALAMUS 10 [hp_X]/59 mL; AGRIMONIA EUPATORIA FLOWER 10 [hp_X]/59 mL; DELPHINIUM STAPHISAGRIA SEED 10 [hp_X]/59 mL; POTASSIUM DICHROMATE 10 [hp_X]/59 mL; SCHOENOCAULON OFFICINALE SEED 10 [hp_X]/59 mL; SEMECARPUS ANACARDIUM JUICE 10 [hp_X]/59 mL
INACTIVE INGREDIENTS: WATER; POTASSIUM SORBATE; CITRIC ACID MONOHYDRATE

Balance

Active ingredients

Adrenalinum, Adrenocorticotrophin (30X, 100X), Agrimonia eup flos, Anacardium, Antimon crud, Calc carb, Castanea sativa flos, Cortisone aceticum, Fucus, Hypothalamus, Kali bic, Oleander, Pituitarum popsterium, Sabadilla, Staphysag, Thyroidinum.

Purpose

Equal volumes of each HPUS ingredient in 10X, 30X, 100X, 1LM, 2LM, 3LM, 5LM potencies, unless otherwise noted.

Uses

for symptoms contributing to: excessive appetite, cravings, overeating, constitutional tendency to gain fat, obesity, water retention.

Warnings

Stop use and ask your doctor if symptoms persist or worsen.

PREGNANCY OR BREAST FEEDING

If pregnant or breast-feeding, take only on advice of a healthcare professional.

Keep out of reach of children.

Directions

- Initially, depress pump until primed.
- Spray one dose directly into mouth.
- Adults 12 & up: 3 sprays 3 times per day.
- Consult a physician for use in children under 12 years of age.
- Use addtiionally as needed, up to 6 times per day.

STORAGE AND HANDLING

Tamper resistant for your protection. Use only if seal is intact.

Claims based on traditional homeopathic practice, not accepted medical evidence. These uses have not been evaluated by the FDA, and product has not been clinically tested.

Inactive ingredients

pure water, citric acid, potassium sorbate

PACKAGE LABEL

EATactics

well on your way

Balance

Professional Homeopathic Formula

Pure Water Base, Gluten Free

Less than 1% Alcohol

2 fl oz (59 mL)